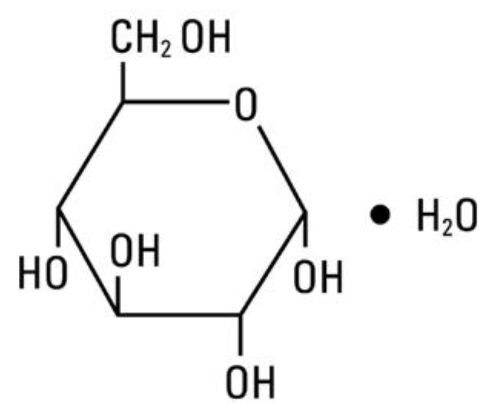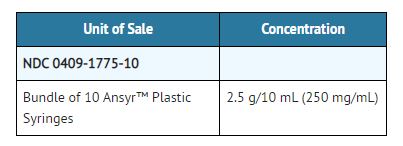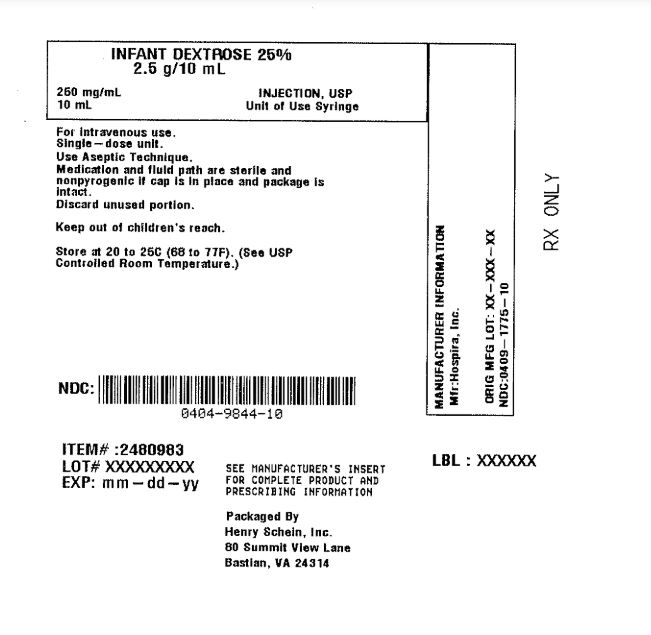 DRUG LABEL: Infant Dextrose 
NDC: 0404-9844 | Form: INJECTION, SOLUTION
Manufacturer: Henry Schein, Inc.
Category: prescription | Type: HUMAN PRESCRIPTION DRUG LABEL
Date: 20251027

ACTIVE INGREDIENTS: Dextrose Monohydrate 250 mg/1 mL

Infant Dextrose 25% 250 mg/mL Injection, USP 10 mL PreFilled Syringe

Description

25% Dextrose Injection, USP is a sterile, nonpyrogenic, hypertonic solution of dextrose in water for injection administered by intravenous injection to restore blood glucose levels in hypoglycemia and as a source of carbohydrate calories. Each milliliter (mL) of fluid contains dextrose, hydrous, 250 mg which delivers 3.4 kcal/gram (0.85 kcal/mL). The solution has an osmolarity of 1.39 mOsmol/mL (calc.). pH is 4.5 (3.2 to 6.5). May contain hydrochloric acid and sodium hydroxide for pH adjustment. The solution contains no bacteriostat, antimicrobial agent or added buffer (except for pH adjustment) and is intended only for use as a single-dose injection. When smaller doses are required the unused portion should be discarded with the entire unit.
25% Dextrose Injection, USP is a dextrose (glucose) and nutrient (carbohydrate) replenisher. Dextrose, USP is chemically designated D-glucose monohydrate, (C6H12O6• H2O), a hexose sugar freely soluble in water.
It has the following structural formula:

The syringe is molded from a specially formulated polypropylene. Water permeates from inside the container at an extremely slow rate which will have an insignificant effect on solution concentration over the expected shelf life. Solutions in contact with the plastic container may leach out certain chemical components from the plastic in very small amounts; however, biological testing was supportive of the safety of the syringe material.

Clinical Pharmacology

When administered intravenously, this solution restores blood glucose levels in hypoglycemia and provides a source of carbohydrate calories. Carbohydrate in the form of dextrose may aid in minimizing liver glycogen depletion and exerts a protein-sparing action. Dextrose injection undergoes oxidation to carbon dioxide and water. 25% Dextrose Injection, USP provides a concentrated solution sufficiently nonirritating for slow intravenous injection to infants for terminating acute symptomatic episodes of hypoglycemia in the neonate and in older infants (fasting blood glucose below 40 mg/100 mL). Values as low as 20 mg/100 mL are not uncommon in normal asymptomatic infants the first few days of life (longer in premature infants).
Symptoms of hypoglycemia in the newborn and small infants may be difficult to evaluate and convulsions often are the first or only recognized manifestation of depressed blood glucose levels. Because of widely varied etiology, the precise cause may be difficult to establish. Hypoglycemia (deficient blood glucose) due to organic or functional hyperinsulinism, may be only temporarily abated by administration of dextrose (glucose) and may rebound to hypoglycemia levels as release of additional insulin is evoked. In addition to various other causes, an idiopathic form of hypoglycemia in infancy has been described, as well as occasional transitory hypoglycemia in the neonatal period which disappears in later infancy. Fetal hyperinsulinism in response to maternal hyperglycemia of diabetic mothers has been observed. Occasionally convulsions associated with severe hypoglycemia are observed in infants of diabetic mothers.
Since glucose is the only sugar utilized for metabolic requirements of human neural tissue, it is essential to restore deficient blood glucose levels from any cause in order to prevent or correct central nervous system dysfunction.

Indications and Usage

25% Dextrose Injection is indicated in the treatment of acute symptomatic episodes of hypoglycemia in the neonate or older infant to restore depressed blood glucose levels and control symptoms. Other drugs, such as epinephrine and glucagon, should be considered in patients unresponsive or intolerant to dextrose (glucose). Oral feeding of dextrose may be necessary in infants with frequently recurring hypoglycemic episodes or to prevent recurrences due to hyperinsulinemia.
25% Dextrose Injection also provides a minimal source of carbohydrate calories.

Contraindications

A concentrated dextrose solution should not be used when intracranial or intraspinal hemorrhage is present.

Warnings

25% Dextrose Injection, USP is hypertonic and may cause phlebitis and thrombosis at the site of injection.
Significant hyperglycemia and possible hyperosmolar syndrome may result from too rapid administration. The physician should be aware of the symptoms of hyperosmolar syndrome, such as loss of consciousness.

Precautions

Frequent monitoring of serum glucose concentrations is required when intravenous dextrose is given to pediatric patients, particularly neonates and low birth weight infants. Do not administer unless the solution is clear and seal is intact. Discard unused portion. Solutions containing dextrose should be used with caution in infants of diabetic mothers except as may be indicated in neonates who are hypoglycemic.
Care should be exercised to insure that the needle is well within the lumen of the vein and that extravasation does not occur. If thrombosis should occur during administration, the injection should be stopped and corrective measures instituted.
Concentrated dextrose solutions should not be administered subcutaneously or intramuscularly.

Carcinogenesis, Mutagenesis, Impairment of Fertility:
Studies with 25% dextrose solutions in polypropylene syringes have not been performed to evaluate carcinogenic potential, mutagenic potential or effects on fertility.

Pregnancy Category C.
Animal reproduction studies have not been conducted with dextrose. It is also not known whether dextrose can cause fetal harm when administered to a pregnant woman or can affect reproduction capacity. Dextrose should be given to a pregnant woman only if clearly needed.

Adverse Reactions

Hyperosmolar syndrome, resulting from excessively rapid administration of concentrated dextrose may cause mental confusion and/or loss of consciousness.
Reactions which may occur because of the solution or the technique of administration include febrile response, infection at the site of injection, venous thrombosis or phlebitis extending from the site of injection and extravasation.
If an adverse reaction does occur, discontinue the infusion, evaluate the patient, institute appropriate therapeutic countermeasures, and save the remainder of the fluid for examination if deemed necessary.

Overdosage

In the event of overdosage (hyperglycemia) during therapy, re-evaluate the patient and institute appropriate corrective measures. See WARNINGS and PRECAUTIONS.

Dosage and Administration

When possible, glucose concentrations of greater than 12% should be administered by central vein to reduce the risk for phlebitis and thrombosis. 25% Dextrose Injection, USP is administered only by slow intravenous injection. The dosage and constant infusion rate of intravenous dextrose must be selected with caution, particularly in neonates and low birth
weight infants, because of the increased risk of hyperglycemia/ hypoglycemia. In the neonate, an injection of 250 to 500 mg (1 to 2 mL)/kg/dose (5 to 10 mL of 25% dextrose in a 5 kg infant) is recommended to control acute symptomatic hypoglycemia (tremors, convulsions,etc.). Larger or repeated single doses (up to 10 or 12 mL of 25% dextrose) may be required in severe cases or older infants. A specimen for blood glucose determination should be taken before injecting the dextrose. In such emergencies, dextrose should be administered promptly without awaiting pretreatment test results. Subsequent continuous intravenous infusion of 10% dextrose injection may be needed to stabilize blood glucose levels. Further treatment should be guided by evaluation of the underlying disorder. Parenteral drug products should be inspected visually for particulate matter and discoloration prior to administration, whenever solution and container permit. See PRECAUTIONS.

How Supplied

25% Dextrose Injection, USP is supplied in single-dose containers as follows:

Store at 20 to 25°C (68 to 77°F). [See USP Controlled Room Temperature.]

Product repackaged by: Henry Schein, Inc., Bastian, VA 24314
From Original Manufacturer/Distributor's NDC and Unit of Sale | To Henry Schein Repackaged Product NDC and Unit of Sale | Total Strength/Total Volume (Concentration) per unit
NDC 0409-1775-10 Bundle of 10 Ansyr™ Plastic Syringes Single-dose containers | NDC 0404-9844-10 1 10 mL Single-dose syringe in a bag (Syringe bears NDC 0409-1775-40) | 2.5 g/10 mL (250 mg/mL)

Distributed by Hospira, Inc., Lake Forest, IL 60045 USA

LAB-1057-4.0

Revised: August 2020